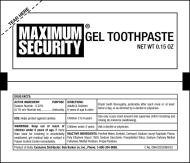 DRUG LABEL: Maxixum Security Gel Toothpaste
NDC: 68747-6028 | Form: PASTE, DENTIFRICE
Manufacturer: Dabur India Limited
Category: otc | Type: HUMAN OTC DRUG LABEL
Date: 20080825

ACTIVE INGREDIENTS: SODIUM FLUORIDE 2.2 mg/1 g
INACTIVE INGREDIENTS: WATER; SORBITOL; CARBOMER HOMOPOLYMER TYPE C; SODIUM LAURYL SULFATE; POLYETHYLENE GLYCOL 1500; SACCHARIN SODIUM; SILICON DIOXIDE; CARBOXYMETHYLCELLULOSE SODIUM; METHYLPARABEN; PROPYLPARABEN

MAXIMUM SECURITY® GEL TOOTHPASTE

NET WT 0.15 OZ

ACTIVE INGREDIENT

Sodium fluoride- 0.22% (0.1% w/v fluoride ion)

PURPOSE

Anticavity.

USE

Helps protect against cavities.

WARNINGS

Keep out of reach of children under 6 years of age. If more than used for brushing is accidentally swallowed, get medical help or contact a Poison Control Center immediately.

DIRECTIONS:

Adults & Children 6 years of age & older:

Brush teeth thoroughly, preferably after each meal or at least twice a day, or as directed by a dentist or physician.

Children 2 to 6 years:

Use only a pea sized amount and supervise child's brushing and rinsing (to minimize swallowing).

Children under 2 years:

Ask a dentist or physician.

INACTIVE INGREDIENTS

Purified Water, Sorbitol, Carbopol, Sodium Lauryl Sulphate, Flavor, Poly Ethylene Glycol 1500, Sodium Saccharin, Precipitated Silica, Sodium Carboxy Methyl Cellulose, Methyl Paraben, Propyl Paraben.

Product of India,
Exclusive Distributor:
Bob Barker Co. Inc.,
Phone: 1-800-334-9880.
Expires: 3 years from the Date of Mfg.

C.No. DNH/COS/DNH/52
Mfg. Date & Batch No. on crimp.

24.06.2009

MAXIMUM SECURITY GEL TOOTHPASTE
ACTIVE INGREDIENT: SODIUM FLUORIDE - 0.22 %
(0.1% w/v fluoride Ion)
SR. NO. INGREDIENTS

1. Treated water
2. Sorbitol
3. Carbopol
4. Sodium lauryl sulphate
5. Flavor
6. Polyethylene glycol 1500
7. Sodium saccharin
8. Precipitated Silica
9. Sodium Carboxy Methyl Cellulose
10. Methyl Paraben
11. Propyl Paraben

PACKAGE LABEL

Principal Display Panel

Packet Label
TEAR HERE
MAXIMUM SECURITY®
GEL TOOTHPASTE
NET WT 0.15 OZ